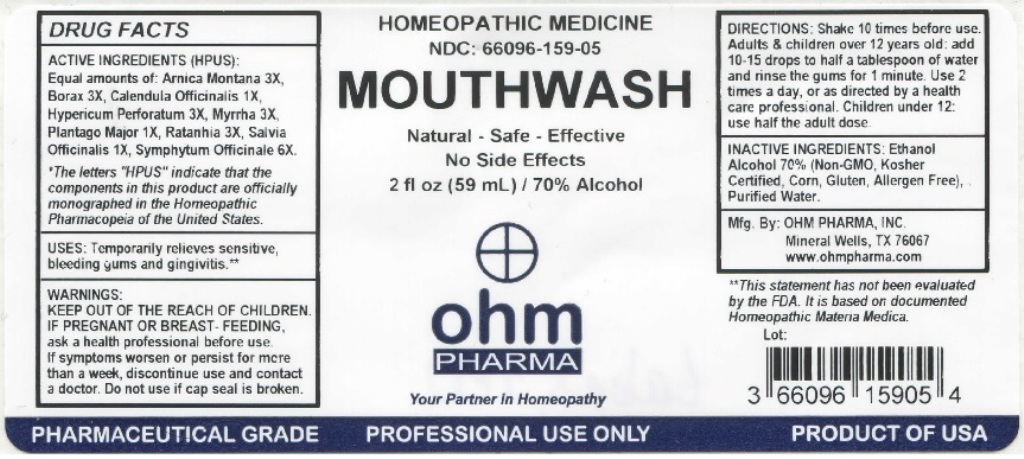 DRUG LABEL: OHM Mouthwash
NDC: 66096-159 | Form: LIQUID
Manufacturer: OHM PHARMA INC.
Category: homeopathic | Type: HUMAN PRESCRIPTION DRUG LABEL
Date: 20211229

ACTIVE INGREDIENTS: ARNICA MONTANA 3 [hp_X]/59 mL; SODIUM BORATE 3 [hp_X]/59 mL; CALENDULA OFFICINALIS FLOWERING TOP 1 [hp_X]/59 mL; HYPERICUM PERFORATUM 3 [hp_X]/59 mL; MYRRH 3 [hp_X]/59 mL; PLANTAGO MAJOR 1 [hp_X]/59 mL; KRAMERIA LAPPACEA ROOT 3 [hp_X]/59 mL; SAGE 1 [hp_X]/59 mL; COMFREY ROOT 6 [hp_X]/59 mL
INACTIVE INGREDIENTS: ALCOHOL; WATER

OHM Mouthwash

ACTIVE INGREDIENT

ACTIVE INGREDIENTS (HPUS): Equal amounts of: Arnica Montana 3X, Borax 3X, Calendula Officinalis 1X, Hypericum Perforatum 3X, Myrrha 3X, Plantago Major 1X, Ratanhia 3X, Salvia Officinalis 1X, Symphytum Officinale 6X.

* The letters "HPUS" indicate that the components in this product are officially monographed in the Homeopathic Pharmacopeia of the United States.

INDICATIONS AND USAGE

USES: Temporarily relieves sensitive, bleeding gums and gingivitis.**

**This statement has not been evaluated by the FDA. It is based on documented Homeopathic Materia Medica.

WARNINGS

WARNINGS: IF PREGNANT OR BREAST-FEEDING, ask a health professional before use. If symptoms worsen or persist for more than a week, discontinue use and contact a doctor.

- KEEP OUT OF THE REACH OF CHILDREN.

DOSAGE AND ADMINISTRATION

DIRECTIONS: Shake 10 times before use. Adults & children over 12 years old: add 10-15 drops to half a tablespoon of water and rinse the gums for 1 minute. Use 2 times a day, or as directed by a health care professional. Children under 12: use half the adult dose.

Do not use if cap seal is broken.

INACTIVE INGREDIENT

INACTIVE INGREDIENTS: Ethanol Alcohol 70% (Non-GMO, Kosher Certified, Corn, Gluten, Allergen Free), Purified Water.

QUESTIONS

Mfg. By: OHM PHARMA, INC. Mineral Wells, TX 76067

www.ohmpharma.com

PACKAGE LABEL

HOMEOPATHIC MEDICINE

NDC: 66096-159-05

MOUTHWASH

Natural - Safe - Effective

No Side Effects

2 fl oz (59mL) / 70% Alcohol

PRODUCT OF USA

PURPOSE

Temporarily relieves sensitive, bleeding gums and gingivitis.